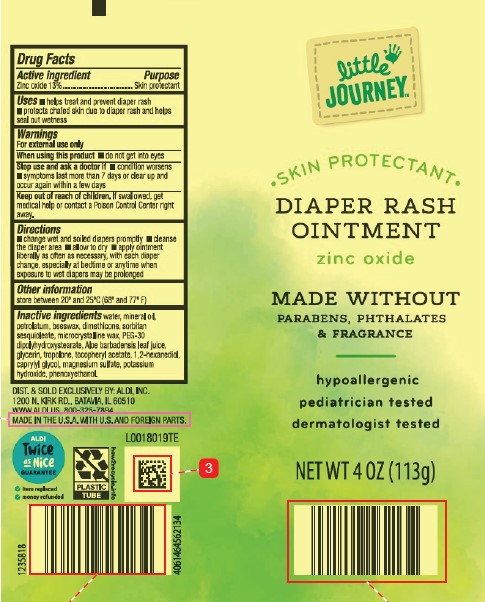 DRUG LABEL: Zinc oxide
NDC: 64024-226 | Form: CREAM
Manufacturer: Aldi, Inc
Category: otc | Type: HUMAN OTC DRUG LABEL
Date: 20260129

ACTIVE INGREDIENTS: ZINC OXIDE 130 mg/1 g
INACTIVE INGREDIENTS: WATER; MINERAL OIL; PETROLATUM; YELLOW WAX; DIMETHICONE; SORBITAN SESQUIOLEATE; MICROCRYSTALLINE WAX; PEG-30 DIPOLYHYDROXYSTEARATE; ALOE VERA LEAF; GLYCERIN; TROPOLONE; .ALPHA.-TOCOPHEROL ACETATE; 1,2-HEXANEDIOL; CAPRYLYL GLYCOL; MAGNESIUM SULFATE MONOHYDRATE; POTASSIUM HYDROXIDE; PHENOXYETHANOL

Little Journey 226.002/226AD
Creamy Diaper Rash Ointment

Active ingredient

Zinc oxide 13%

Purpose

Skin protectant

Uses

- helps treat and prevent diaper rash
- protects chafed skin due to diaper rash and helps seal out wetness

Warnings

For external use only

When using this product

- do not get into eyes

Stop use and ask a doctor if

- condition worsens
- symptoms last more than 7 days or clear up and occur again within a few days

Keep out of reach of children.

If swallowed, get medical help or contact a Poison Control Center right away.

Directions

- change wet and soiled diaper promplty
- cleanse the diaper area
- allow to dry
- apply ointment liberally as often as necessary, with each diaper change, especially at bedtime or anytime when exposure to wet diapers may be prolonged

Other information

store between 20º and 25ºC (68º and 77ºF).

Inactive ingredients

water, mineral oil, petrolatum, beeswax, dimethicone, sorbitan sesquioleate, microcrystalline wax, PEG-30 dipolyhydroxystearate, Aloe barbadensis leaf juice, glycerin, tropolone, tocopheryl acetate, 1,2-hexanediol, caprylyl glycol, magnesium sulfate, potassium hydroxide, phenoxyethanol

ADVERSE REACTION

DIST. & SOLD EXCLUSIVELY BY: ALDI, INC.

1200 N. Kirk RD. BATAVIA, IL 60510

WWW.ALDI.US. 800-325-7894

MADE IN THE U.S.A. WITH U.S. AND FOREIGN PARTS.

ALDI TWICE as Nice GUARANTEE

- item replaced
- money refunded

PLASTIC TUBE

how2recycle.info

Principal display panel

Little Journey™

SKIN PROTECTANT

DIAPER RASH OINTMENT

zinc oxide

MADE WITHOUT PARABANS, PHTHALATES & FRAGRANCE

hypoallergenic

pediatrician tested

dermatologist tested

NET WT 4 OZ (113 g)